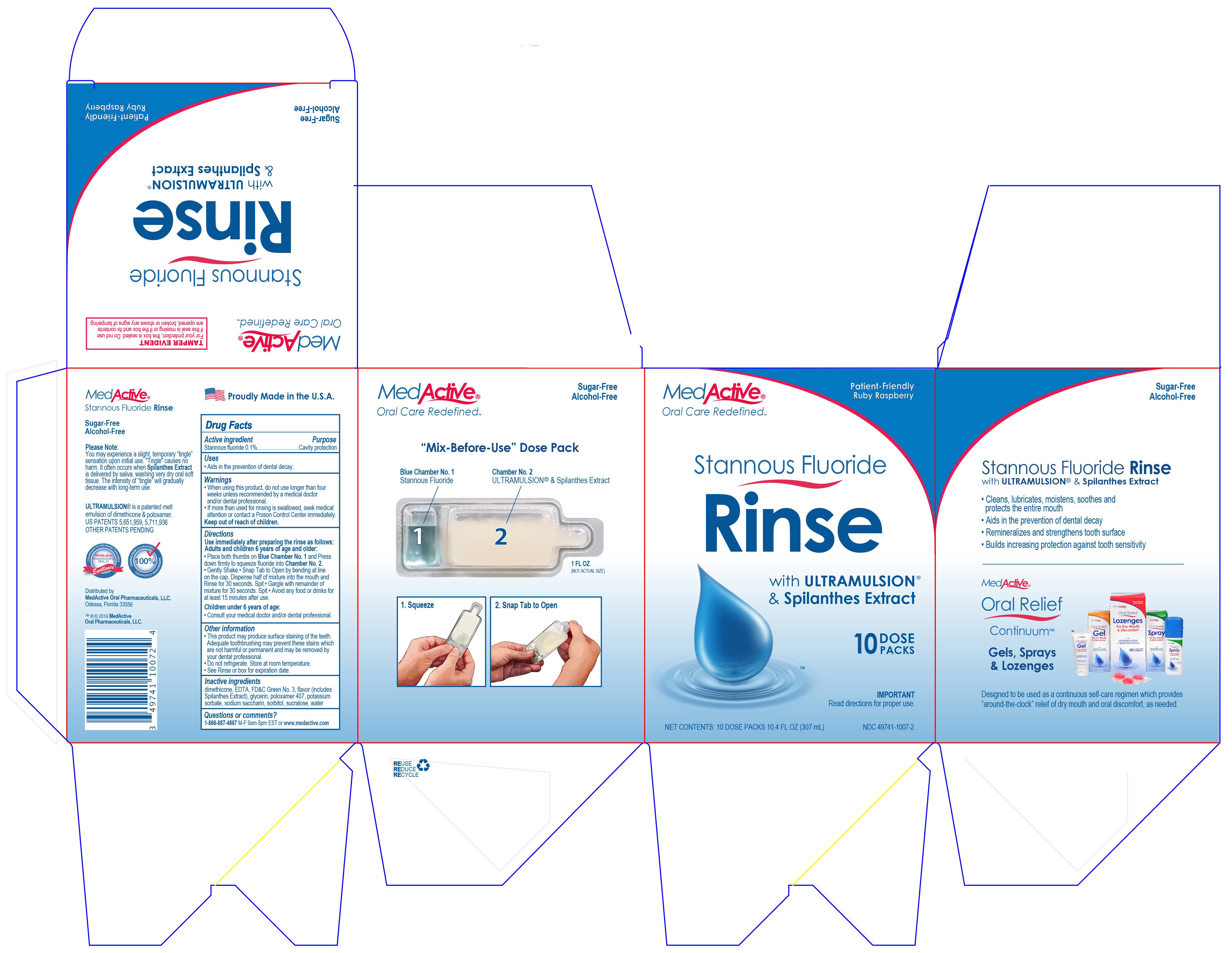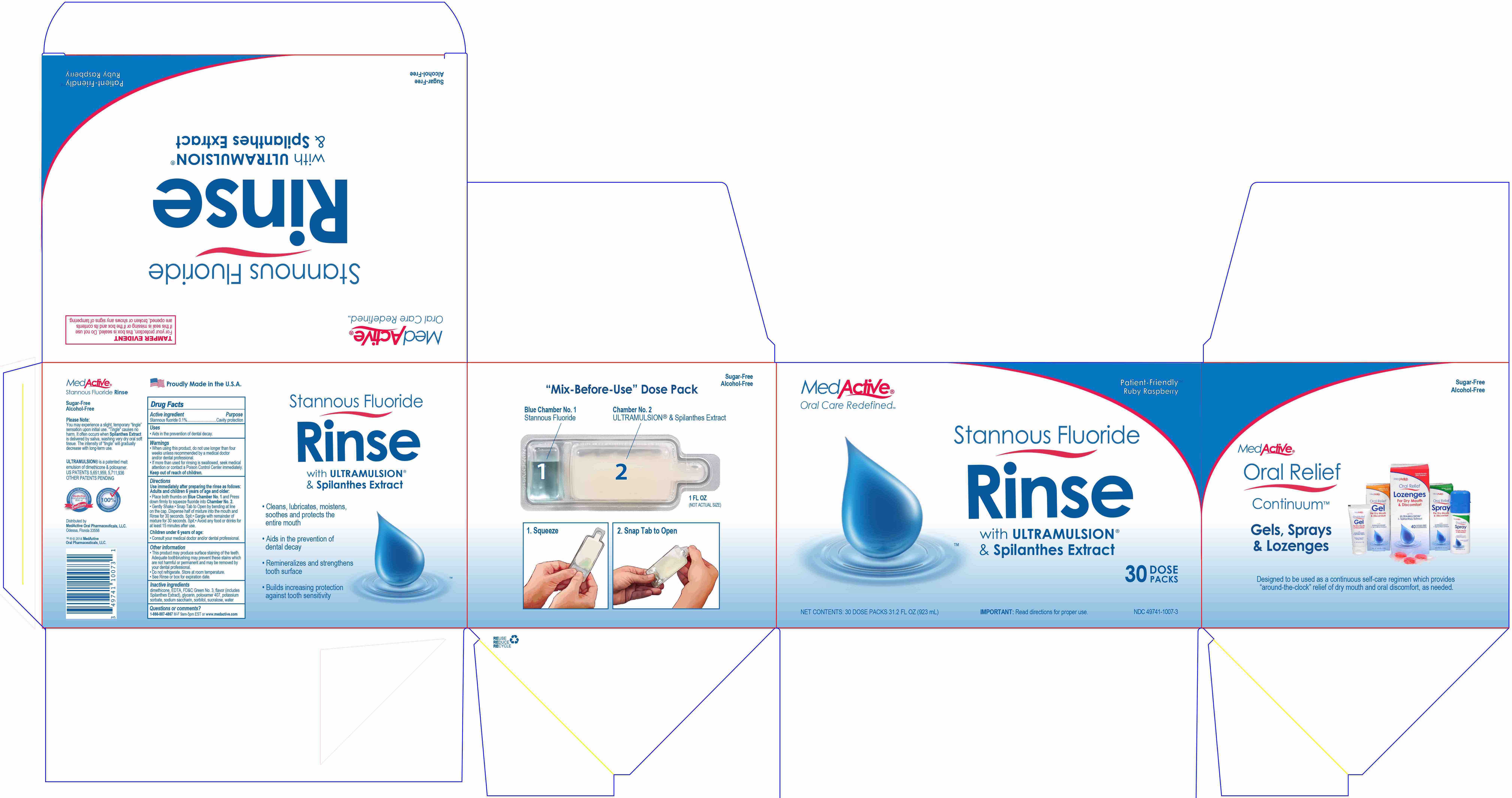 DRUG LABEL: MedActive Patient Friendly
NDC: 49741-1007 | Form: KIT | Route: ORAL
Manufacturer: Integrate Oral Care, LLC.
Category: otc | Type: HUMAN OTC DRUG LABEL
Date: 20211230

ACTIVE INGREDIENTS: STANNOUS FLUORIDE 6.3 mg/1 mL
INACTIVE INGREDIENTS: FD&C GREEN NO. 3 1 mL/1 mL; GLYCERIN 1 mL/1 mL; SACCHARIN SODIUM; SORBITOL; DIMETHICONE; POTASSIUM SORBATE; POLOXAMER 407; SUCRALOSE; WATER; EDETIC ACID

Active ingredient

Stannous fluoride 0.1%

Purpose

Cavity protection

Uses

- Aids in the prevention of dental decay.

Warnings

- When using this product, do not use longer than four weeks unless recommended by a medical doctor and/or dental professional.
- If more than used for rinsing is swallowed, seek medical attention or contact a Poison Control Center immediately.

Keep out of reach of children.

Directions

Use immediately after preparing the rinse as follows:

Adults and children 6 years of age and older:

- Place both thumbs on Blue Chamber No. 1 and Press down firmly to squeeze fluoride into Chamber No. 2.
- Gently Shake.
- Snap Tab to Open by bending at line on the cap. Dispense half of mixture into the mouth and Rinse for 30 seconds. Spit.
- Gargle with remainder of mixture for 30 seconds. Spit.
- Avoid any food or drinks for at least 15 minutes after use.

Children under 6 years of age:

- Consult your medical doctor and/or dental professional

Other information

- This product may produce surface staining of the teeth.
- Adequate toothbrushing may prevent these stains which are not harmful or permanent and may be removed by your dental professional.
- Do not refrigerate. Store at room temperature.

Inactive Ingredients

dimethicone, EDTA, FD&C Green No. 3, flavor (includes Spilathes Extract), glycerin, poloxamer 407, potassium sorbate, sodium saccharin, sorbitol, sucralose, water

Questions or comments?

1-866-877-4867 M-F 9am-5pm EST or www.medactive.com

PACKAGE LABEL

MedActive® Oral Care Redefined™

Patient-Friendly™ Ruby Raspberry

Stannous Fluoride Rinse with ULTRAMULSION® & Spilanthes Extract

10 DOSE PACKS

IMPORTANT Read directions for proper use.

NET CONTENTS: 10 DOSE PACKS 10.4 FL OX (307 mL)

NDC 49741-1007-2

PACKAGE LABEL

MedActive® Oral Care Redefined™

Patient-Friendly™ Ruby Raspberry

Stannous Fluoride Rinse with ULTRAMULSION® & Spilanthes Extract

30 DOSE PACKS

IMPORTANT: Read directions for proper use.

NDC 49741-1007-3